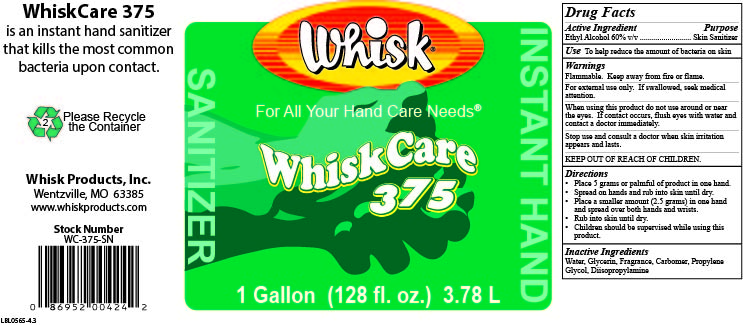 DRUG LABEL: WhiskCare 375
NDC: 65585-375 | Form: GEL
Manufacturer: Whisk Products, Inc.
Category: otc | Type: HUMAN OTC DRUG LABEL
Date: 20251111

ACTIVE INGREDIENTS: ALCOHOL 600 mL/1 L
INACTIVE INGREDIENTS: DIISOPROPYLAMINE; PROPYLENE GLYCOL; CARBOMER INTERPOLYMER TYPE A (ALLYL SUCROSE CROSSLINKED); WATER; GLYCERIN

WhiskCare 375

Active Ingredient

Ethyl Alcohol 60% v/v

Purpose

Skin Sanitizer

Use

To help reduce the amount of bacteria on skin

Warnings

Flammable. Keep away from fire or flame.

For external use only. If swallowed, seek medical attention.

When using this product do not use around or near the eyes. If contact occurs, flush eyes with water and contact a doctor immediately.

Stop use and consult a doctor when skin irritation appears and lasts.

KEEP OUT OF REACH OF CHILDREN.

Directions

- Place 5 grams or palmful of product in one hand.
- Spread on hands and rub into skin until dry.
- Place a smaller amount (2.5 grams) in one hand and spread over both hands and wrists.
- Rub into skin until dry.
- Children should be supervised while using this product.

Inactive Ingredients

Water, Glycerin, Fragrance, Carbomer, Propylene Glycol, Diisopropylamine